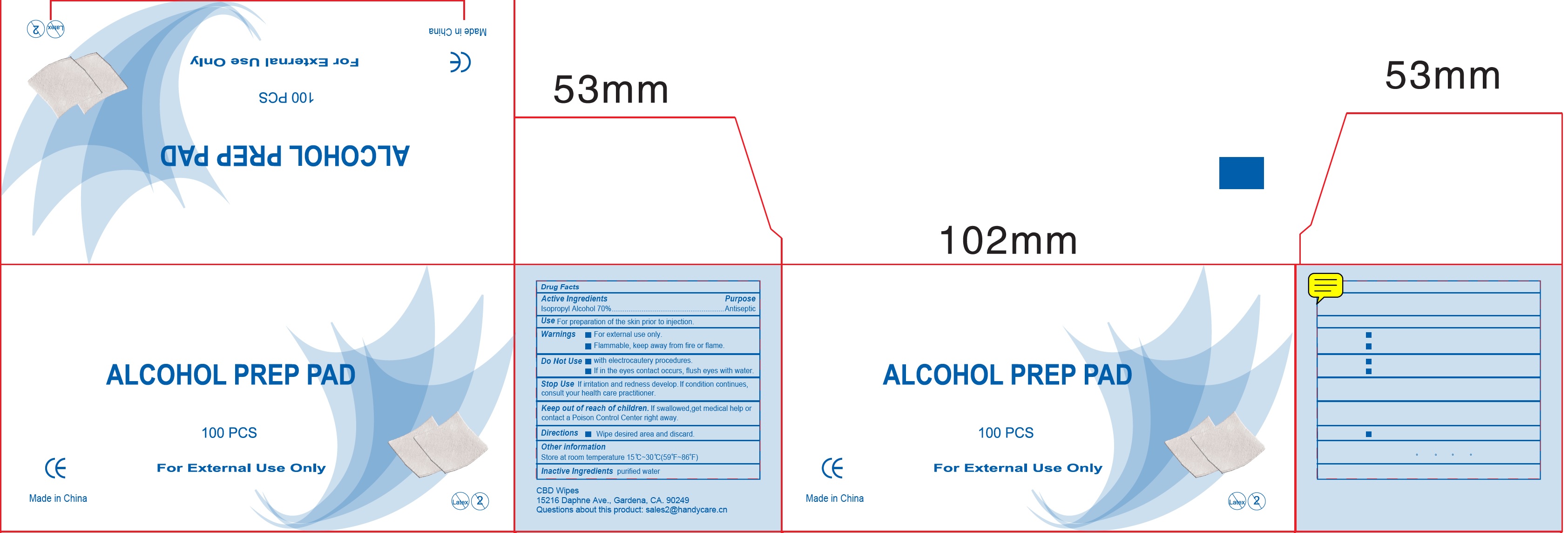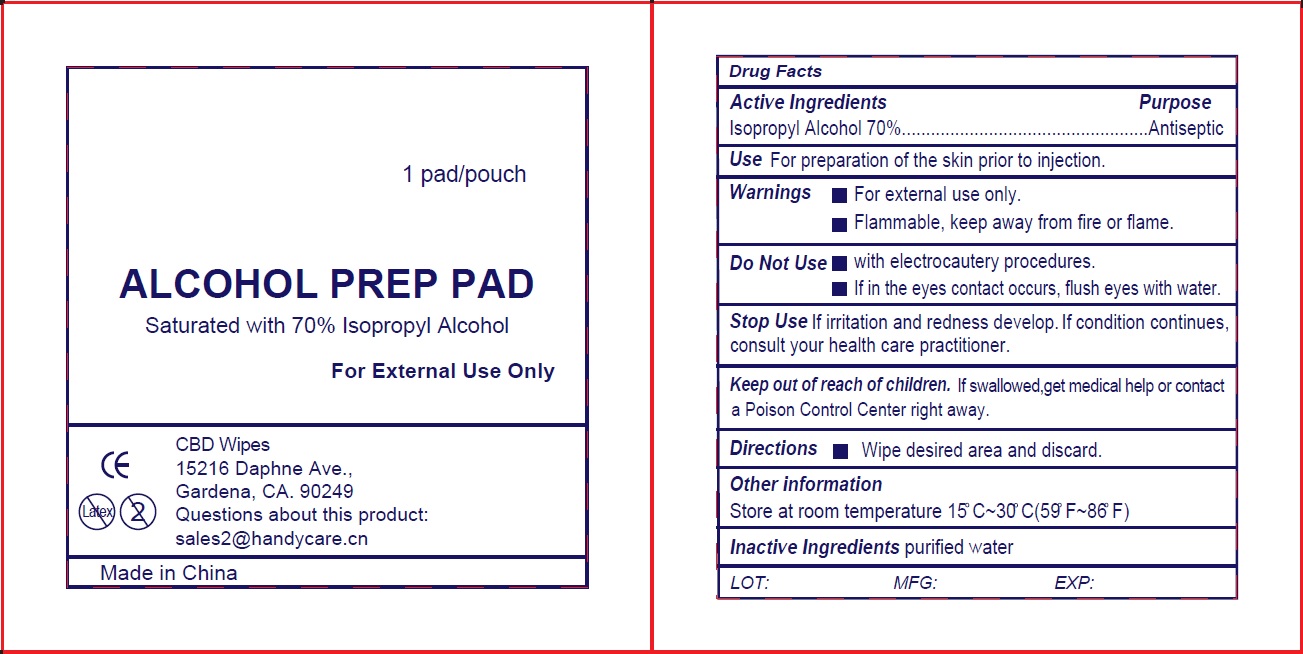 DRUG LABEL: Alcohol Prep
NDC: 73161-000 | Form: CLOTH
Manufacturer: Handy Care Ltd. DBA CBD Wipes
Category: otc | Type: HUMAN OTC DRUG LABEL
Date: 20200925

ACTIVE INGREDIENTS: ISOPROPYL ALCOHOL 700 mg/1 mL
INACTIVE INGREDIENTS: WATER

Alcohol Wipes

Active Ingredients

Isopropyl Alcohol 70%

Purpose

Antiseptic

Use

For preparation of the skin prior to injection.

Warnings

- For external use only.
- Flammable, keep away from fire or flame.

Do Not Use

- with electrocautery procedures.
- If in the eyes contact occurs, flush eyes with water.

Stop Use

If irritation and redness develop. If condition continues, consult your health care practitioner.

Keep out of reach of children.

If swallowed,get medical help or contact a Poison Control Center right away.

Directions

- Wipe desired area and discard.

Other information

Store at room temperature 15° C~30° C(59° F~86° F)

Inactive Ingredients

purified water